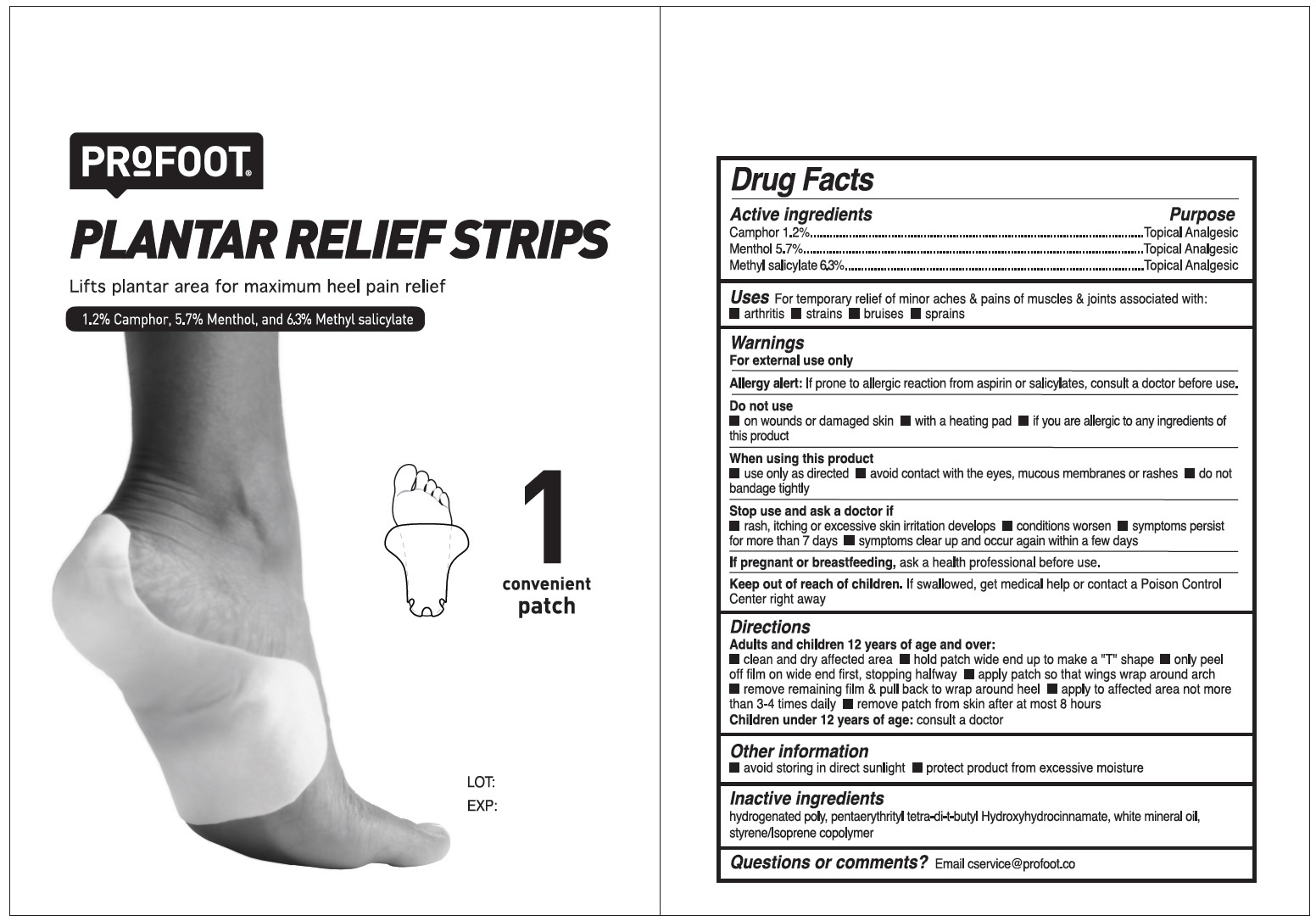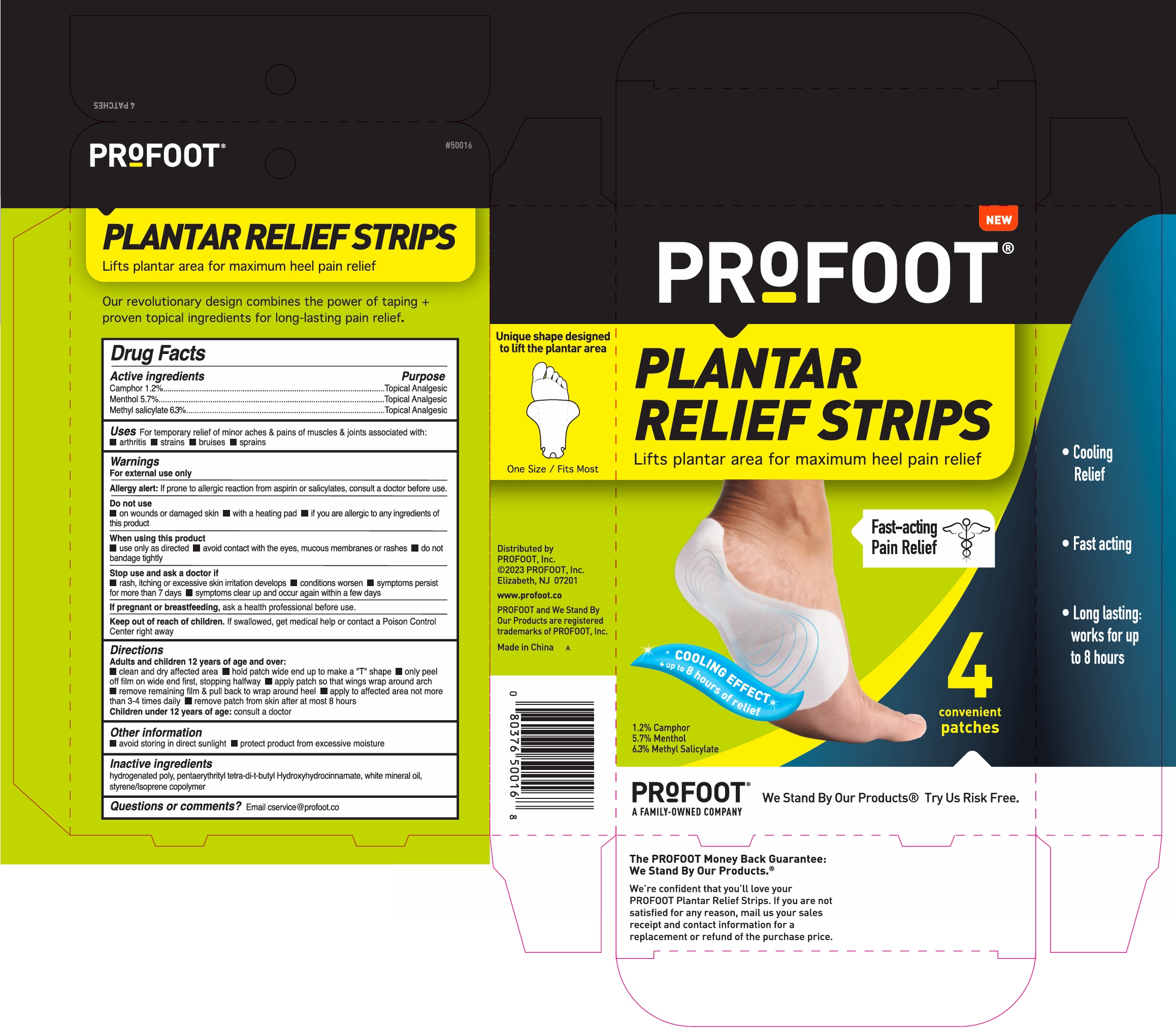 DRUG LABEL: Profoot Plantar Relief Strips
NDC: 29784-602 | Form: PATCH
Manufacturer: Rooftop Consumer Health, Inc.
Category: otc | Type: HUMAN OTC DRUG LABEL
Date: 20241023

ACTIVE INGREDIENTS: CAMPHOR (NATURAL) 12 mg/1 g; MENTHOL 57 mg/1 g; METHYL SALICYLATE 63 mg/1 g
INACTIVE INGREDIENTS: PENTAERYTHRITOL TETRAKIS(3-(3,5-DI-TERT-BUTYL-4-HYDROXYPHENYL)PROPIONATE); MINERAL OIL

Profoot Plantar Relief Strips

Active ingredients

Camphor 1.2%

Menthol 5.7%

Methyl salicylate 6.3%

Purpose

Topical Analgesic

Uses

For temporary relief of minor aches & pains of muscles & joints associated with: • arthritis • strains • bruises • sprains

Warnings

For external use only

Allergy alert:If prone to allergic reaction from aspirin or salicylates, consult a doctor before use.

Do not use

• on wounds or damaged skin • with a heating pad • if you are allergic to any ingredients of this product

When using this product

• use only as directed • avoid contact with the eyes, mucocus membranes or rashes • do not bandage tightly

Stop use and ask a doctor if

• rash, itching or excessive skin irritation develops • condtions worsen • symtomps persist for more than 7 days • symptoms clean up and occur again within a few days

If pregnant or reach of children.

If swallowed, get medical help or contact a Poison Control Center right away

Keep out of reach of children.

If swallowed, get medical help or contact a Poison Control Center right away

Directions

Adults and children 12 years of age and over:

• clean and dry affected area • hold patch wide end up to make a "I" shape • only peel off film on wide end first, stopping halfway • apply patch so that wings wrap around arch •remove remaing film & pull back to wrap around heel • apply to affected area not more than 3-4 times daily • remove patch from skin after at most 8 hours

Children under 12 years of age:consult a doctor

Other information

• avoid storing in direct sunlight • protect product from excessive moisture

Inactive ingredients

hydrogenated poly, pentaerythrityl tetra-di-t-butyl Hydroxyhydrocinnamate, white mineral oil, styrene/Isoprene copolymer

Questions or comments?

Email cservice@profoot.co